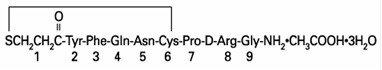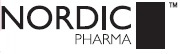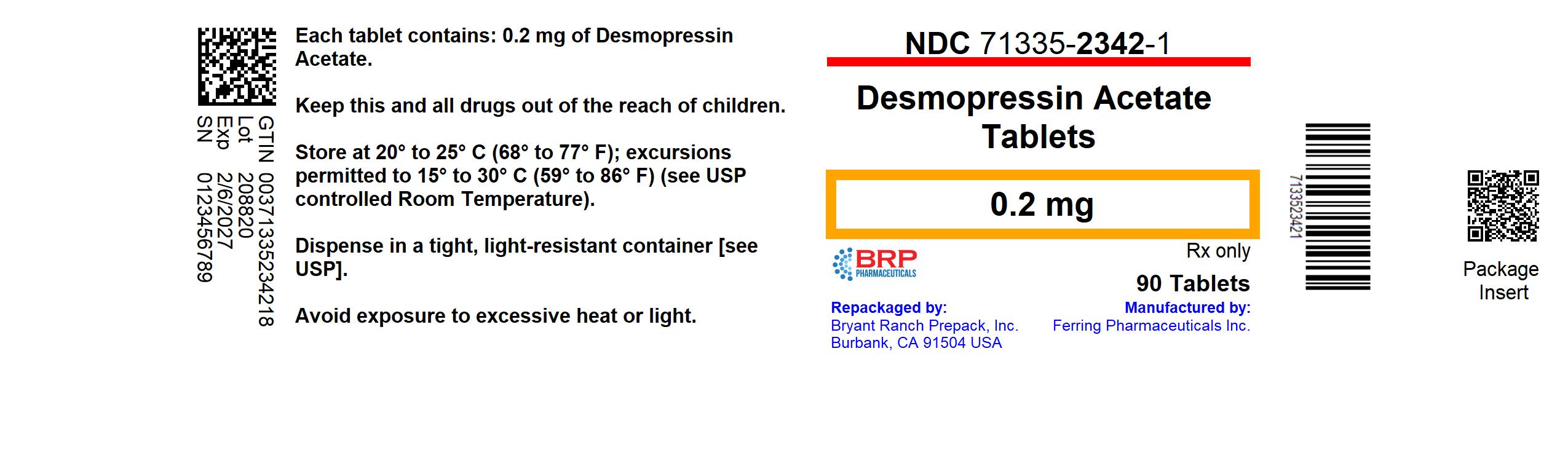 DRUG LABEL: Desmopressin Acetate
NDC: 71335-2342 | Form: TABLET
Manufacturer: Bryant Ranch Prepack
Category: prescription | Type: HUMAN PRESCRIPTION DRUG LABEL
Date: 20250131

ACTIVE INGREDIENTS: DESMOPRESSIN ACETATE 0.2 mg/1 1
INACTIVE INGREDIENTS: LACTOSE, UNSPECIFIED FORM; STARCH, POTATO; MAGNESIUM STEARATE; POVIDONE, UNSPECIFIED

Desmopressin Acetate Tablets
Rx only

DESCRIPTION

Desmopressin Acetate Tablets (desmopressin acetate) are a synthetic analogue of the natural pituitary hormone 8-arginine vasopressin (ADH), an antidiuretic hormone affecting renal water conservation. It is chemically defined as follows:

Mol. Wt. 1183.34 Empirical Formula: C46H64N14O12S2•C2H4O2•3H2O

1-(3-mercaptopropionic acid)-8-D-arginine vasopressin monoacetate (salt) trihydrate.

Desmopressin Acetate Tablets contain either 0.1 or 0.2 mg desmopressin acetate. Inactive ingredients include: lactose, potato starch, magnesium stearate and povidone.

CLINICAL PHARMACOLOGY

Desmopressin Acetate Tablets contain as active substance, desmopressin acetate, a synthetic analogue of the natural hormone arginine vasopressin.

Central Diabetes Insipidus: Dose response studies in patients with diabetes insipidus have demonstrated that oral doses of 0.025 mg to 0.4 mg produced clinically significant antidiuretic effects. In most patients, doses of 0.1 mg to 0.2 mg produced optimal antidiuretic effects lasting up to eight hours. With doses of 0.4 mg, antidiuretic effects were observed for up to 12 hours; measurements beyond 12 hours were not recorded. Increasing oral doses produced dose dependent increases in the plasma levels of desmopressin acetate.

The plasma half-life of desmopressin acetate followed a monoexponential time course with t1/2 values of 1.5 to 2.5 hours which was independent of dose.

The bioavailability of Desmopressin Acetate oral tablets is about 5% compared to intranasal desmopressin acetate, and about 0.16% compared to intravenous desmopressin acetate. The time to reach maximum plasma desmopressin acetate levels ranged from 0.9 to 1.5 hours following oral or intranasal administration, respectively. Following administration of Desmopressin Acetate Tablets, the onset of antidiuretic effect occurs at around 1 hour, and it reaches a maximum at about 4 to 7 hours based on the measurement of increased urine osmolality.

The use of Desmopressin Acetate Tablets in patients with an established diagnosis will result in a reduction in urinary output with an accompanying increase in urine osmolality. These effects usually will allow resumption of a more normal life style, with a decrease in urinary frequency and nocturia.

There are reports of an occasional change in response to the intranasal formulations of desmopressin acetate (Desmopressin Acetate Nasal Spray and Desmopressin Acetate Rhinal Tube). Usually, the change occurred over a period of time greater than six months. This change may be due to decreased responsiveness, or to shortened duration of effect. There is no evidence that this effect is due to the development of binding antibodies, but may be due to a local inactivation of the peptide. No lessening of effect was observed in the 46 patients who were treated with Desmopressin Acetate Tablets for 12 to 44 months and no serum antibodies to desmopressin were detected.

The change in structure of arginine vasopressin to desmopressin acetate resulted in less vasopressor activity and decreased action on visceral smooth muscle relative to enhanced antidiuretic activity. Consequently, clinically effective antidiuretic doses are usually below the threshold for effects on vascular or visceral smooth muscle. In the four long-term studies of Desmopressin Acetate Tablets, no increases in blood pressure in 46 patients receiving Desmopressin Acetate Tablets for periods of 12 to 44 months were reported. In one study, the pharmacodynamic characteristics of Desmopressin Acetate Tablets and intranasal formulation were compared during an 8-hour dosing interval at steady state. The doses administered to 36 hydrated (water loaded) healthy male adult volunteers every 8 hours were 0.1, 0.2, 0.4 mg orally and 0.01 mg intranasally by rhinal tube. The results are shown in the following table:

Mean Changes from Baseline (SE) in Pharmacodynamic Parameters in Normal Healthy Adult Volunteers
Treatment | Total Urine Volume in mL | Maximum Urine Osmolality in mOsm/kg
0.1 mg PO q8h | -3689.3 (149.6) | 514.8 (21.9)
0.2 mg PO q8h | -4429.9 (149.6) | 686.3 (21.9)
0.4 mg PO q8h | -4998.8 (149.6) | 769.3 (21.9)
0.01 mg IN q8h | -4844.9 (149.6) | 754.1 (21.9)
(SE) = Standard error of the mean

With respect to the mean values of total urine volume decrease and maximum urine osmolality increase from baseline, the 90% confidence limits estimated that the 0.4 mg and 0.2 mg oral dose produced between 95% and 110% and 84% to 99% of pharmacodynamic activity, respectively, when compared to the 0.01 mg intranasal dose.

While both the 0.2 mg and 0.4 mg oral doses are considered pharmacodynamically similar to the 0.01 mg intranasal dose, the pharmacodynamic data on an inter-subject basis was highly variable and, therefore, individual dosing is recommended.

In another study in diabetes insipidus patients, the pharmacodynamic characteristics of Desmopressin Acetate Tablets and intranasal formulations were compared over a 12-hour period. Ten fluid-controlled patients under age 18 were administered tablet doses of 0.2 mg and 0.4 mg, and intranasal doses of 0.01 mg and 0.02 mg.

Mean Peak Pharmacodynamic Parameters (SD) in Pediatric and Adolescent Diabetes Insipidus Patients
Treatment | Urine Volume in mL/min | Maximum Urine Osmolality in mOsm/kg
0.01 mg IN | 0.3 (0.15) | 717.0 (224.63)
0.02 mg IN | 0.3 (0.25) | 761.8 (298.82)
0.2 mg PO | 0.3 (0.12) | 678.3 (147.91)
0.4 mg PO | 0.2 (0.15) | 787.2 (73.34)
(SD) = Standard Deviation

All four dose formulations (0.01 mg IN, 0.02 mg IN, 0.2 mg PO and 0.4 mg PO) have a similar, pronounced pharmacodynamic effect on urine volume and urine osmolality. At two hours after study drug administration, mean urine volume was 4 mL/min and urine osmolality was >500 mOsm/kg. Mean plasma osmolality remained relatively constant over the time course recorded (0 to 12 hours). A statistical separation from baseline did not occur at any dose or time point. In these patients, the 0.2 mg tablets and the 0.01 mg intranasal spray exhibited similar pharmacodynamic profiles as did the 0.4 mg tablets and the 0.02 mg intranasal spray formulation. In another study of adult diabetes insipidus patients previously controlled on Desmopressin Acetate Intranasal Spray, after one week of self-titration from spray to tablets, patients’ diuresis was controlled with 0.1 mg Desmopressin Acetate Tablets three times a day.

Primary Nocturnal Enuresis: Two double-blind, randomized, placebo-controlled studies were conducted in 340 patients with primary nocturnal enuresis. Patients were 5-17 years old, and 72% were males. A total of 329 patients were evaluated for efficacy. Patients were evaluated over a two-week baseline period in which the average number of wet nights was 10 (range 4-14). Patients were then randomized to receive 0.2, 0.4, or 0.6 mg of Desmopressin Acetate Tablets or placebo. The pooled results after two weeks are shown in the following table:

Response to Desmopressin Acetate Tablets and Placebo at Two Weeks of Treatment Mean (SE) Number of Wet Nights/2 Weeks
 | Placebo (n = 85) | 0.2 mg/day (n = 79) | 0.4 mg/day (n = 82) | 0.6 mg/day (n = 83)
Baseline | 10 (0.3) | 11 (0.3) | 10 (0.3) | 10 (0.3)
Reduction from Baseline | 1 (0.3) | 3 (0.4) | 3 (0.4) | 4 (0.4)
Percent Reduction from Baseline | 10% | 27% | 30% | 40%
p-value vs placebo | ---- | <0.05 | <0.05 | <0.05

Patients treated with Desmopressin Acetate Tablets showed a statistically significant reduction in the number of wet nights compared to placebo-treated patients. A greater response was observed with increasing doses up to 0.6 mg.

In a six month, open-label extension study, patients completing the placebo-controlled studies were started on 0.2 mg/day Desmopressin Acetate Tablets, and the dose was progressively increased until the optimal response was achieved (maximum dose 0.6 mg/day). A total of 230 patients were evaluated for efficacy; the average number of wet nights/2 weeks during the untreated baseline period was 10 (range 4-14), and the average duration (SD) of treatment was 4.2 (1.8) months. Twenty-five (25) patients (11%) achieved a complete or near complete response (≤2 wet nights/2 weeks) and did not require titration to the 0.6 mg/day dose. The majority of patients (198 of 230, 86%) were titrated to the highest dose. When all dose groups were combined, 128 (56%) showed at least a 50% reduction from baseline in the number of wet nights/2 weeks, while 87 (38%) patients achieved a complete or near complete response.

PHARMACOKINETICS

Human Pharmacokinetics: Desmopressin acetate is mainly excreted in the urine. A pharmacokinetic study conducted in healthy volunteers and patients with mild, moderate, and severe renal impairment (n=24, 6 subjects in each group) receiving single dose desmopressin acetate (2 mcg) injection demonstrated a difference in desmopressin acetate terminal half-life. Terminal half-life significantly increased from 3 hours in normal healthy patients to 9 hours in patients with severe renal impairment. (See CONTRAINDICATIONS.)

INDICATIONS AND USAGE

Central Diabetes Insipidus: Desmopressin Acetate Tablets are indicated as antidiuretic replacement therapy in the management of central diabetes insipidus and for the management of the temporary polyuria and polydipsia following head trauma or surgery in the pituitary region. Desmopressin acetate is ineffective for the treatment of nephrogenic diabetes insipidus.

Patients were selected for therapy based on the diagnosis by means of the water deprivation test, the hypertonic saline infusion test, and/or response to antidiuretic hormone. Continued response to desmopressin acetate can be monitored by measuring urine volume and osmolality.

Primary Nocturnal Enuresis: Desmopressin Acetate Tablets are indicated for the management of primary nocturnal enuresis. Desmopressin Acetate Tablets may be used alone or as an adjunct to behavioral conditioning or other non-pharmacologic intervention.

CONTRAINDICATIONS

Desmopressin Acetate Tablets are contraindicated in individuals with known hypersensitivity to desmopressin acetate or to any of the components of Desmopressin Acetate Tablets.

Desmopressin acetate is contraindicated in patients with moderate to severe renal impairment (defined as a creatinine clearance below 50 mL/min).

Desmopressin acetate is contraindicated in patients with hyponatremia or a history of hyponatremia.

WARNINGS

1. Very rare cases of hyponatremia have been reported from world-wide postmarketing experience in patients treated with desmopressin acetate. Desmopressin acetate is a potent antidiuretic which, when administered, may lead to water intoxication and/or hyponatremia. Unless properly diagnosed and treated hyponatremia can be fatal. Therefore, fluid restriction is recommended and should be discussed with the patient and/or guardian. Careful medical supervision is required.

2. When Desmopressin Acetate Tablets are administered, in particular in pediatric and geriatric patients, fluid intake should be adjusted downward to decrease the potential occurrence of water intoxication and hyponatremia. (See PRECAUTIONS, Pediatric Use and Geriatric Use.) All patients receiving desmopressin acetate therapy should be observed for the following signs of symptoms associated with hyponatremia: headache, nausea/vomiting, decreased serum sodium, weight gain, restlessness, fatigue, lethargy, disorientation, depressed reflexes, loss of appetite, irritability, muscle weakness, muscle spasms or cramps and abnormal mental status such as hallucinations, decreased consciousness and confusion. Severe symptoms may include one or a combination of the following: seizure, coma and/or respiratory arrest. Particular attention should be paid to the possibility of the rare occurrence of an extreme decrease in plasma osmolality that may result in seizures which could lead to coma.

3. Desmopressin acetate should be used with caution in patients with habitual or psychogenic polydipsia who may be more likely to drink excessive amounts of water, putting them at greater risk of hyponatremia.

PRECAUTIONS

GENERAL PRECAUTIONS

General: Intranasal formulations of desmopressin acetate at high doses and Desmopressin Acetate Injection have infrequently produced a slight elevation of blood pressure which disappears with a reduction of dosage. Although this effect has not been observed when single oral doses up to 0.6 mg have been administered, the drug should be used with caution in patients with coronary artery insufficiency and/or hypertensive cardiovascular disease, because of a possible rise in blood pressure.

Desmopressin acetate should be used with caution in patients with conditions associated with fluid and electrolyte imbalance, such as cystic fibrosis, heart failure and renal disorders because these patients are prone to hyponatremia.

Rare severe allergic reactions have been reported with desmopressin acetate. Anaphylaxis has been reported rarely with intravenous and intranasal administration of desmopressin acetate but not with Desmopressin Acetate Tablets.

LABORATORY TESTS

Laboratory Tests: Central Diabetes Insipidus: Laboratory tests for monitoring the patient with central diabetes insipidus or post-surgical or head trauma-related polyuria and polydipsia include urine volume and osmolality. In some cases, measurements of plasma osmolality may be useful.

DRUG INTERACTIONS

Drug Interactions: Although the pressor activity of desmopressin acetate is very low compared to its antidiuretic activity, large doses of Desmopressin Acetate Tablets should be used with other pressor agents only with careful patient monitoring. The concomitant administration of drugs that may increase the risk of water intoxication with hyponatremia, (e.g. tricyclic antidepressants, selective serotonin re-uptake inhibitors, chlorpromazine, opiate analgesics, NSAIDs, lamotrigine and carbamazepine) should be performed with caution.

CARCINOGENESIS AND MUTAGENESIS AND IMPAIRMENT OF FERTILITY

Carcinogenicity, Mutagenicity, Impairment of Fertility: Studies with desmopressin acetate have not been performed to evaluate carcinogenic potential, mutagenic potential or effects on fertility.

PREGNANCY

Pregnancy: Category B: Fertility studies have not been done. Teratology studies in rats and rabbits at doses from 0.05 to 10 mcg/ kg/day (approximately 0.1 times the maximum systemic human exposure in rats and up to 38 times the maximum systemic human exposure in rabbits based on surface area, mg/m^2) revealed no harm to the fetus due to desmopressin acetate. There are, however, no adequate and well-controlled studies in pregnant women. Because animal studies are not always predictive of human response, this drug should be used during pregnancy only if clearly needed.

Several publications where desmopressin acetate was used in the management of diabetes insipidus during pregnancy are available; these include a few anecdotal reports of congenital anomalies and low birth weight babies. However, no causal connection between these events and desmopressin acetate has been established. A fifteen year Swedish epidemiologic study of the use of desmopressin acetate in pregnant women with diabetes insipidus found the rate of birth defects to be no greater than that in the general population; however, the statistical power of this study is low. As opposed to preparations containing natural hormones, desmopressin acetate in antidiuretic doses has no uterotonic action and the physician will have to weigh the possible therapeutic advantages against the possible risks in each case.

NURSING MOTHERS

Nursing Mothers: There have been no controlled studies in nursing mothers. A single study in postpartum women demonstrated a marked change in plasma, but little if any change in assayable desmopressin acetate in breast milk following an intranasal dose of 0.01 mg.

It is not known whether the drug is excreted in human milk. Because many drugs are excreted in human milk, caution should be exercised when desmopressin acetate is administered to nursing mothers.

PEDIATRIC USE

Pediatric Use: Central Diabetes Insipidus: Desmopressin Acetate Tablets have been used safely in pediatric patients, age 4 years and older, with diabetes insipidus for periods up to 44 months. In younger pediatric patients the dose must be individually adjusted in order to prevent an excessive decrease in plasma osmolality leading to hyponatremia and possible convulsions; dosing should start at 0.05 mg (1/2 of the 0.1 mg tablet). Use of Desmopressin Acetate Tablets in pediatric patients requires careful fluid intake restrictions to prevent possible hyponatremia and water intoxication. Fluid restriction should be discussed with the patient and/or guardian. (See WARNINGS.)

Primary Nocturnal Enuresis: Desmopressin Acetate Tablets have been safely used in pediatric patients age 6 years and older with primary nocturnal enuresis for up to 6 months. Some patients respond to a dose of 0.2 mg; however, increasing responses are seen at doses of 0.4 mg and 0.6 mg. No increase in the frequency or severity of adverse reactions or decrease in efficacy was seen with an increased dose or duration. The dose should be individually adjusted to achieve the best results. Treatment with desmopressin for primary nocturnal enuresis should be interrupted during acute intercurrent illness characterized by fluid and/or electrolyte imbalance (e.g., systemic infections, fever, recurrent vomiting or diarrhea) or under conditions of extremely hot weather, vigorous exercise or other conditions associated with increased water intake.

GERIATRIC USE

Geriatric Use: Clinical studies of Desmopressin Acetate Tablets did not include sufficient numbers of subjects aged 65 and over to determine whether they respond differently from younger subjects. Other reported clinical experience has not identified differences in responses between the elderly and younger patients. In general, dose selection for an elderly patient should be cautious, usually starting at the low end of the dosing range, reflecting the greater frequency of decreased hepatic, renal, or cardiac function, and of concomitant disease or other drug therapy.

This drug is known to be substantially excreted by the kidney, and the risk of toxic reactions to this drug may be greater in patients with impaired renal function. Because elderly patients are more likely to have decreased renal function, care should be taken in dose selection, and it may be useful to monitor renal function. Desmopressin acetate is contraindicated in patients with moderate to severe renal impairment (defined as a creatinine clearance below 50 mL/min). (See CLINICAL PHARMACOLOGY, Human Pharmacokinetics and CONTRAINDICATIONS.)

Use of Desmopressin Acetate Tablets in geriatric patients requires careful fluid intake restrictions to prevent possible hyponatremia and water intoxication. Fluid restriction should be discussed with the patient. (See WARNINGS.)

ADVERSE REACTIONS

Infrequently, large doses of the intranasal formulations of desmopressin acetate and Desmopressin Acetate Injection have produced transient headache, nausea, flushing and mild abdominal cramps. These symptoms have disappeared with reduction in dosage.

Central Diabetes Insipidus: In long-term clinical studies in which patients with diabetes insipidus were followed for periods up to 44 months of Desmopressin Acetate Tablet therapy, transient increases in AST (SGOT) no higher than 1.5 times the upper limit of normal were occasionally observed. Elevated AST (SGOT) returned to the normal range despite continued use of Desmopressin Acetate Tablets.

Primary Nocturnal Enuresis: The only adverse event occurring in ≥3% of patients in controlled clinical trials with Desmopressin Acetate Tablets that was probably, possibly, or remotely related to study drug was headache (4% desmopressin acetate, 3% placebo).

Other: The following adverse events have been reported; however their relationship to desmopressin acetate has not been established: abnormal thinking, diarrhea, and edema-weight gain.

See WARNINGS for the possibility of water intoxication and hyponatremia.

Post Marketing: There have been rare reports of hyponatremic convulsions associated with concomitant use with the following medications: oxybutinin and imipramine.

OVERDOSAGE

Signs of overdose may include confusion, drowsiness, continuing headache, problems with passing urine and rapid weight gain due to fluid retention. (See WARNINGS.) In case of overdose, the dose should be reduced, frequency of administration decreased, or the drug withdrawn according to the severity of the condition. There is no known specific antidote for desmopressin acetate. The patient should be observed and treated with appropriate symptomatic therapy. An oral LD50 has not been established. Oral doses up to 0.2 mg/kg/day have been administered to dogs and rats for 6 months without any significant drug-related toxicities reported. An intravenous dose of 2 mg/kg in mice demonstrated no effect.

DOSAGE AND ADMINISTRATION

Central Diabetes Insipidus: The dosage of Desmopressin Acetate Tablets must be determined for each individual patient and adjusted according to the diurnal pattern of response. Response should be estimated by two parameters: adequate duration of sleep and adequate, not excessive, water turnover. Patients previously on intranasal desmopressin acetate therapy should begin tablet therapy twelve hours after the last intranasal dose. During the initial dose titration period, patients should be observed closely and appropriate safety parameters measured to assure adequate response. Patients should be monitored at regular intervals during the course of Desmopressin Acetate Tablet therapy to assure adequate antidiuretic response. Modifications in dosage regimen should be implemented as necessary to assure adequate water turnover. Fluid restriction should be observed. (See WARNINGS, PRECAUTIONS, Pediatric Use and Geriatric Use.)

Adults and Children: It is recommended that patients be started on doses of 0.05 mg (1/2 of the 0.1 mg tablet) two times a day and individually adjusted to their optimum therapeutic dose. Most patients in clinical trials found that the optimal dosage range is 0.1 mg to 0.8 mg daily, administered in divided doses. Each dose should be separately adjusted for an adequate diurnal rhythm of water turnover. Total daily dosage should be increased or decreased in the range of 0.1 mg to 1.2 mg divided into two or three daily doses as needed to obtain adequate antidiuresis. See Pediatric Use subsection for special considerations when administering desmopressin acetate to pediatric diabetes insipidus patients.

GERIATRIC USE

Geriatric Use: This drug is known to be substantially excreted by the kidney, and the risk of toxic reactions to this drug may be greater in patients with impaired renal function. Because elderly patients are more likely to have decreased renal function, care should be taken in dose selection, and it may be useful to monitor renal function. (See CLINICAL PHARMACOLOGY, Human Pharmacokinetics, CONTRAINDICATIONS, and PRECAUTIONS, Geriatric Use.)

Primary Nocturnal Enuresis: The dosage of Desmopressin Acetate Tablets must be determined for each individual patient and adjusted according to response. Patients previously on intranasal desmopressin acetate therapy can begin tablet therapy the night following (24 hours after) the last intranasal dose. The recommended initial dose for patients age 6 years and older is 0.2 mg at bedtime. The dose may be titrated up to 0.6 mg to achieve the desired response. Fluid restriction should be observed, and fluid intake should be limited to a minimum from 1 hour before desmopressin acetate administration, until the next morning, or at least 8 hours after administration. (See WARNINGS, PRECAUTIONS, Pediatric Use and Geriatric Use.)

HOW SUPPLIED

Desmopressin Acetate 0.2 mg Tablet

- NDC 71335-2342-1: 90 TABLETs in a BOTTLE

Store at Controlled Room Temperature 20 to 25°C (68 to 77°F) [see USP]. Avoid exposure to excessive heat or light.

This product should be dispensed in a container with a child-resistant cap.

Keep out of the reach of children.

Repackaged/Relabeled by:
Bryant Ranch Prepack, Inc.
Burbank, CA 91504

Manufactured for:
Nordic Pharma, Inc.
Berwyn, PA 19312
www.nordicpharmausa.com

The Nordic Pharma Logo is a trademark of Nordic Group B.V.

Origin Sweden

Rev. 10/2024

2009056650

PACKAGE LABEL

Desmopressin Acetate 0.2 mg Tablet